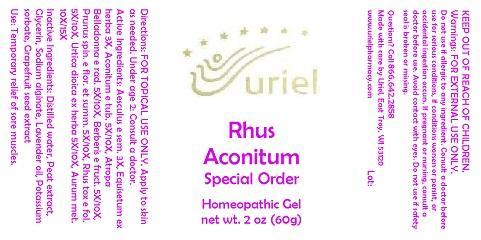 DRUG LABEL: Rhus Aconitum Special Order
NDC: 48951-8249 | Form: GEL
Manufacturer: Uriel Pharmacy Inc.
Category: homeopathic | Type: HUMAN OTC DRUG LABEL
Date: 20140915

ACTIVE INGREDIENTS: HORSE CHESTNUT 3 [hp_X]/1 g; EQUISETUM ARVENSE TOP 3 [hp_X]/1 g; ACONITUM NAPELLUS 5 [hp_X]/1 g; ATROPA BELLADONNA 5 [hp_X]/1 g; BERBERIS VULGARIS ROOT BARK 5 [hp_X]/1 g; SLOE 5 [hp_X]/1 g; TOXICODENDRON PUBESCENS LEAF 5 [hp_X]/1 g; URTICA DIOICA LEAF 5 [hp_X]/1 g; GOLD 10 [hp_X]/1 g
INACTIVE INGREDIENTS: WATER; SPHAGNUM SQUARROSUM PEAT; GLYCERIN; SODIUM ALGINATE; LAVENDER OIL; POTASSIUM SORBATE; CITRUS PARADISI SEED

Rhus Aconitum Special Order

INDICATIONS AND USAGE

Directions: FOR TOPICAL USE ONLY.

DOSAGE AND ADMINISTRATION

Apply to skin as needed. Under age 2: Consult a doctor.

ACTIVE INGREDIENT

Active Ingredients: Aesculus e sem. 3X, Equisetum ex herba 3X, Aconitum e tub. 5X/10X, Atropa Belladonna e rad. 5X/10X, Berberis e fruct. 5X/10X, Prunus spin. e flor. et summ. 5X/10X, Rhus tox e fol. 5X/10X, Urtica dioica ex herba 5X/10X, Aurum met. 10X/15X

INACTIVE INGREDIENT

Inactive Ingredients: Distilled water, Peat extract, Glycerin, Sodium alginate, Lavender oil, Potassium sorbate, Grapefruit seed extract

PURPOSE

Use: Temporary relief of sore muscles.

KEEP OUT OF REACH OF CHILDREN.

WARNINGS

Warnings: FOR EXTERNAL USE ONLY. Do not use if allergic to any ingredient. Consult a doctor before use for serious conditions, if conditions worsen or persist, or accidental ingestion occurs. If pregnant or nursing, consult a doctor before use. Avoid contact with eyes. Do not use if safety seal is broken or missing.

QUESTIONS

Questions? Call 866.642.2858 Made with care by Uriel, East Troy, WI 53120 www.urielpharmacy.com